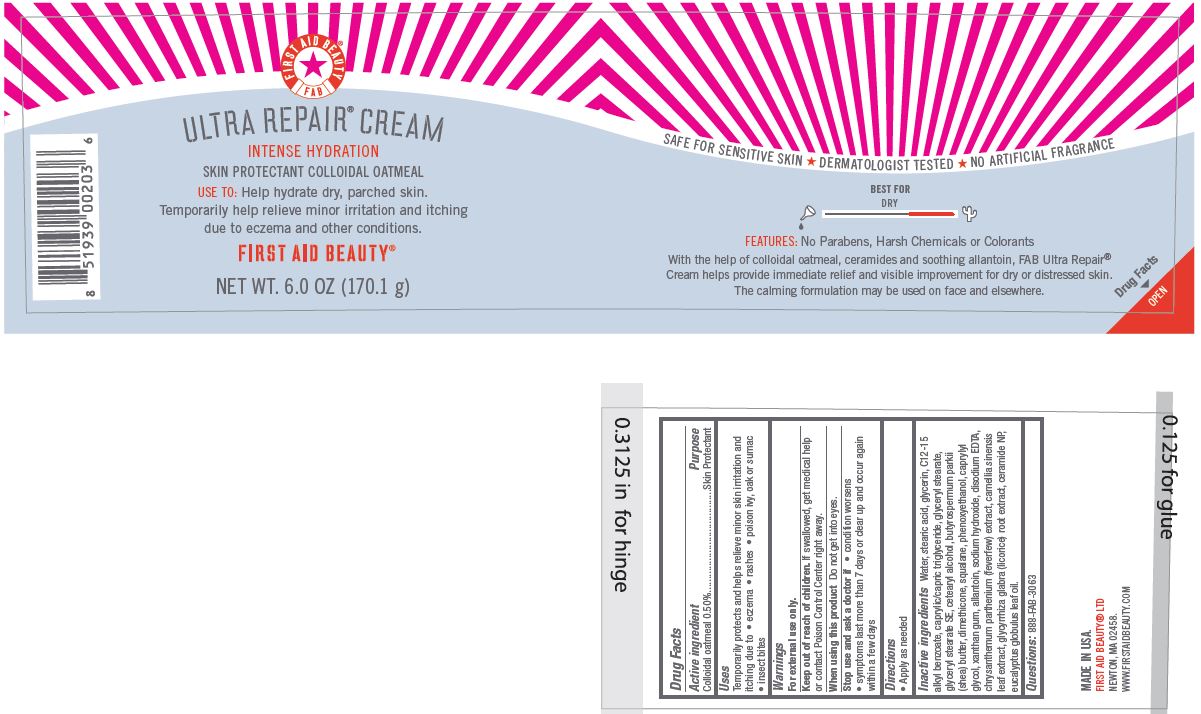 DRUG LABEL: First Aid Beauty FAB Ultra Repair Skin Protectant
NDC: 69423-556 | Form: CREAM
Manufacturer: The Procter & Gamble Manufacturing Company
Category: otc | Type: HUMAN OTC DRUG LABEL
Date: 20251208

ACTIVE INGREDIENTS: OATMEAL 0.5 g/100 g
INACTIVE INGREDIENTS: CERAMIDE NP; CETOSTEARYL ALCOHOL; EUCALYPTUS OIL; SQUALANE; CAPRYLYL GLYCOL; DIMETHICONE; EDETATE DISODIUM; GLYCERYL STEARATE SE; ALKYL (C12-15) BENZOATE; GREEN TEA LEAF; TANACETUM PARTHENIUM FLOWER; SODIUM HYDROXIDE; PHENOXYETHANOL; SHEA BUTTER; GLYCYRRHIZA GLABRA; WATER; GLYCERIN; XANTHAN GUM; ALLANTOIN; GLYCERYL MONOSTEARATE; MEDIUM-CHAIN TRIGLYCERIDES; STEARIC ACID

First Aid Beauty FAB Ultra Repair Cream Skin Protectant

Drug Facts

Active ingredients

Colloidal Oatmeal 0.5%

Purpose

Skin Protectant

Uses

- Temporarily protects and helps relieve minor skin irritation and itching due to eczema, rashes, poison ivy, oak or sumac, insect bites

Warnings

For external use only.

Keep out of reach of children. If swallowed, get medical help or contact a Poison Control Center right away.

WHEN USING

Do not get into eyes.

Stop use and ask a doctor if condition worsens, symptoms last more than 7 days or clear up and occur again within a few days

Directions

Apply as needed

INACTIVE INGREDIENT

Water, stearic acid, glycerin, C12-15 alkyl benzoate, caprylic/capric triglyceride, glyceryl stearate, glyceryl stearate SE, cetearyl alcohol, butyrospermum parkii (shea) butter, dimethicone, squalane, phenoxyethanol, caprylyl glycol, xanthan gum, allantoin, sodium hydroxide, disodium EDTA, chrysanthemum parthenium (feverfew) extract, camellia sinensis leaf extract, glycyrrhiza glabra (licorice) root extract, ceramide NP, eucalyptus globulus leaf oil.

Questions:

888-FAB-3063

MADE IN USA

FIRST AID BEAUTY LTD

NEWTON, MA 02458

WWW.FIRSTAIDBEAUTY.COM

PRINCIPAL DISPLAY PANEL - 170.1 g jar

First Aid Beauty

FAB

Ultra Repair Cream

Intense Hydration

Skin Protectant Colloidal Oatmeal

FIrst Aid Beauty ®

Net Wt. 6.0 oz (170.1 g)